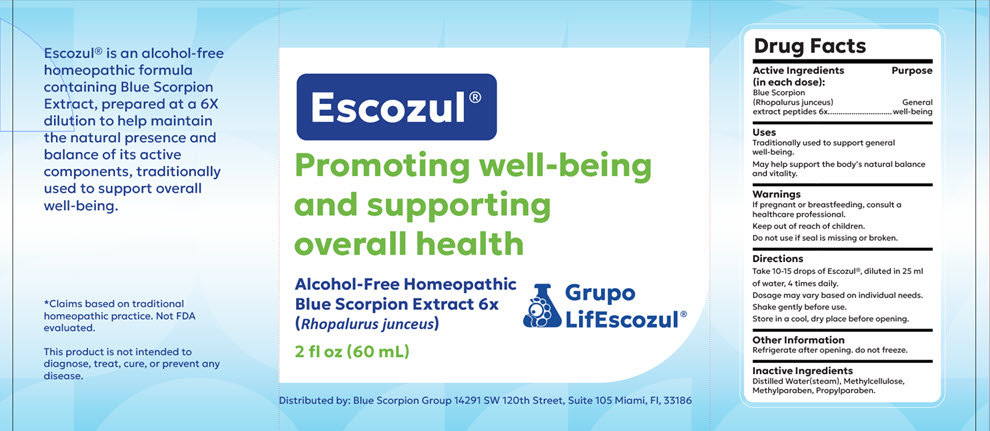 DRUG LABEL: Escozul
NDC: 87019-001 | Form: SOLUTION/ DROPS
Manufacturer: Blue Scorpion Group INC
Category: homeopathic | Type: HUMAN OTC DRUG LABEL
Date: 20250911

ACTIVE INGREDIENTS: RHOPALURUS JUNCEUS VENOM 6 [hp_X]/1 mL
INACTIVE INGREDIENTS: WATER; METHYLCELLULOSE, UNSPECIFIED; METHYLPARABEN; PROPYLPARABEN

Escozul®

Drug Facts

Active Ingredients (in each dose)

Blue Scorpion (Rhopalurus junceus) extract peptides 6x

Purpose

General well-being

Uses

Traditionally used to support general well-being.

May help support the body's natural balance and vitality.

Warnings

PREGNANCY OR BREAST FEEDING

If pregnant or breastfeeding, consult a healthcare professional.

Keep out of reach of children.

Do not use if seal is missing or broken.

Directions

Take 10-15 drops of Escozul®, diluted in 25 ml of water, 4 times daily.

Dosage may vary based on individual needs.

Shake gently before use.

Store in a cool, dry place before opening.

Other information

Refrigerate after opening. do not freeze.

Inactive Ingredients

Distilled Water(steam), Methylcellulose, Methylparaben, Propylparaben.

Distributed by: Blue Scorpion Group 14291 SW 120th Street, Suite 105 Miami, Fl, 33186

PRINCIPAL DISPLAY PANEL - 60 mL Bottle Label

Escozul®

Promoting well-being
and supporting
overall health

Alcohol-Free Homeopathic
Blue Scorpion Extract 6x
(Rhopalurus junceus)

Grupo
LifEscozul®

2 fl oz (60 mL)